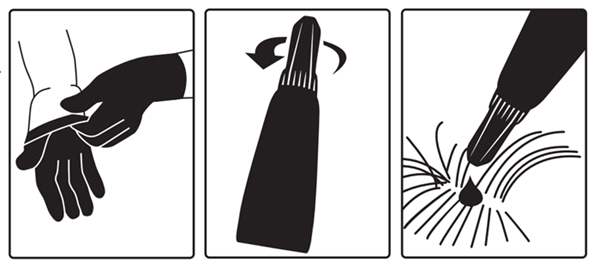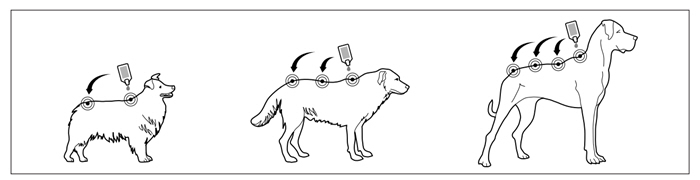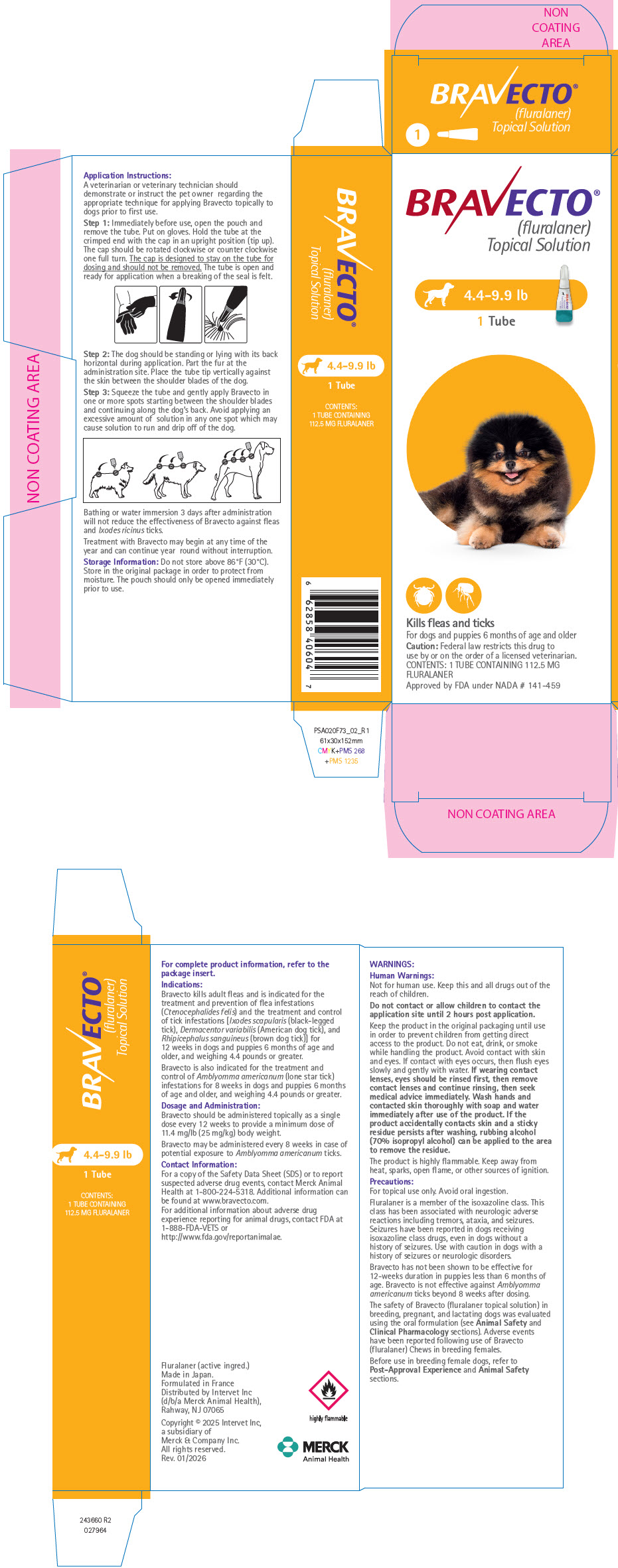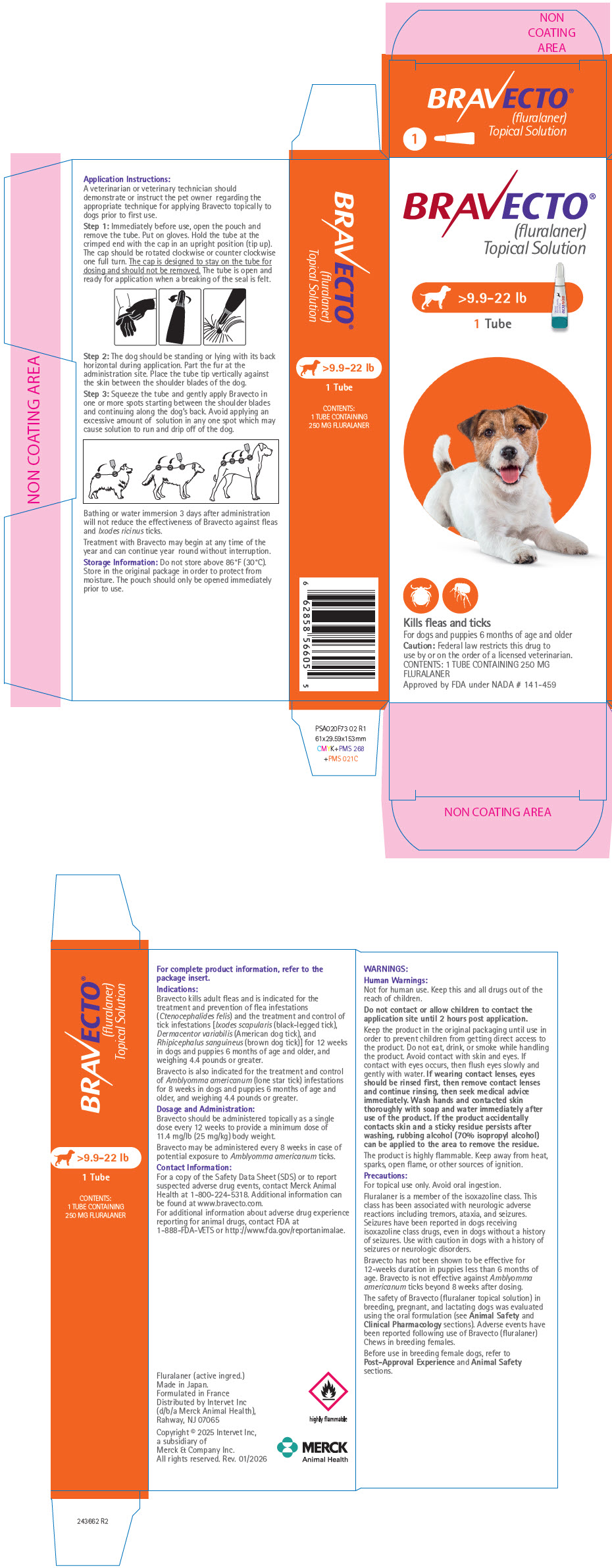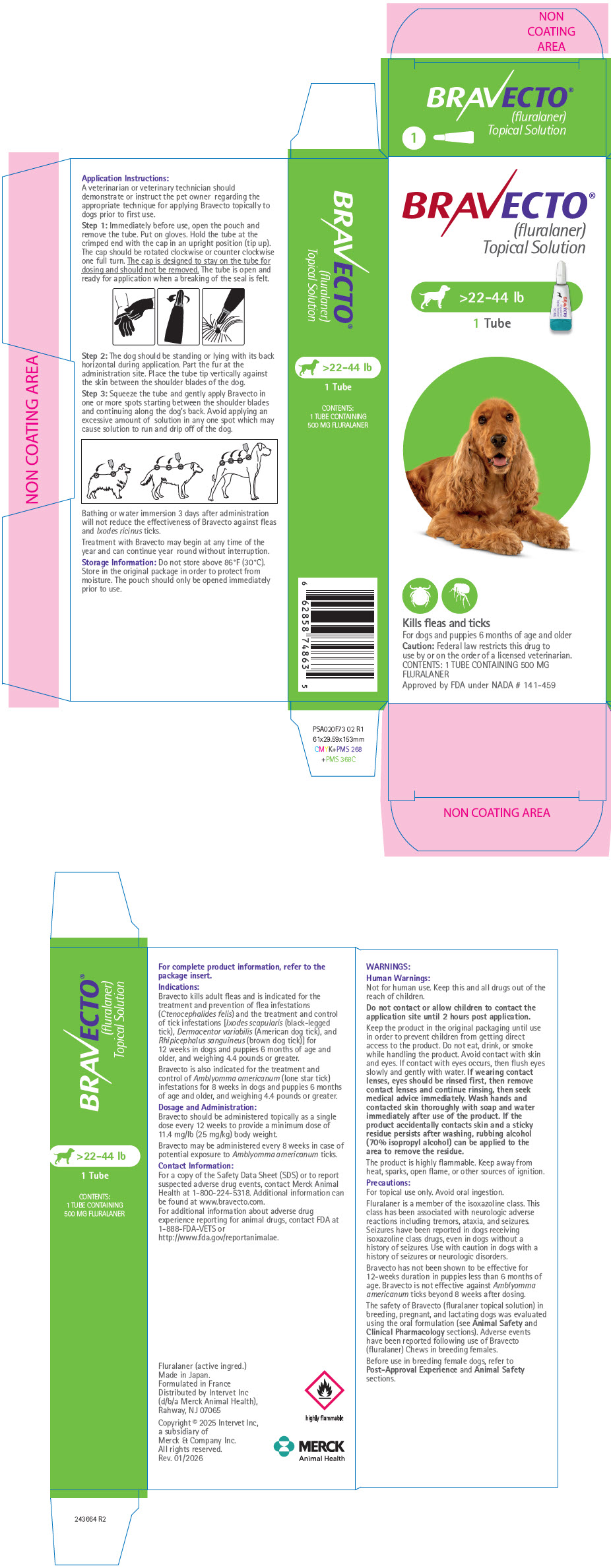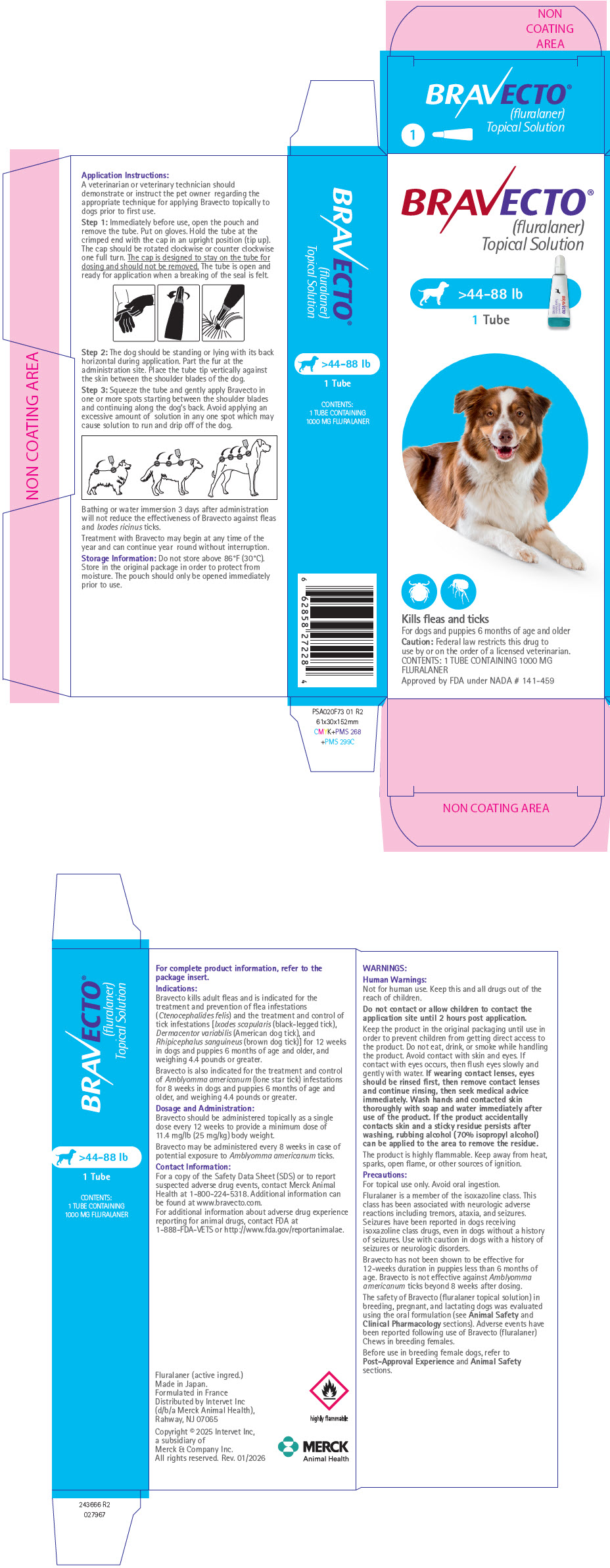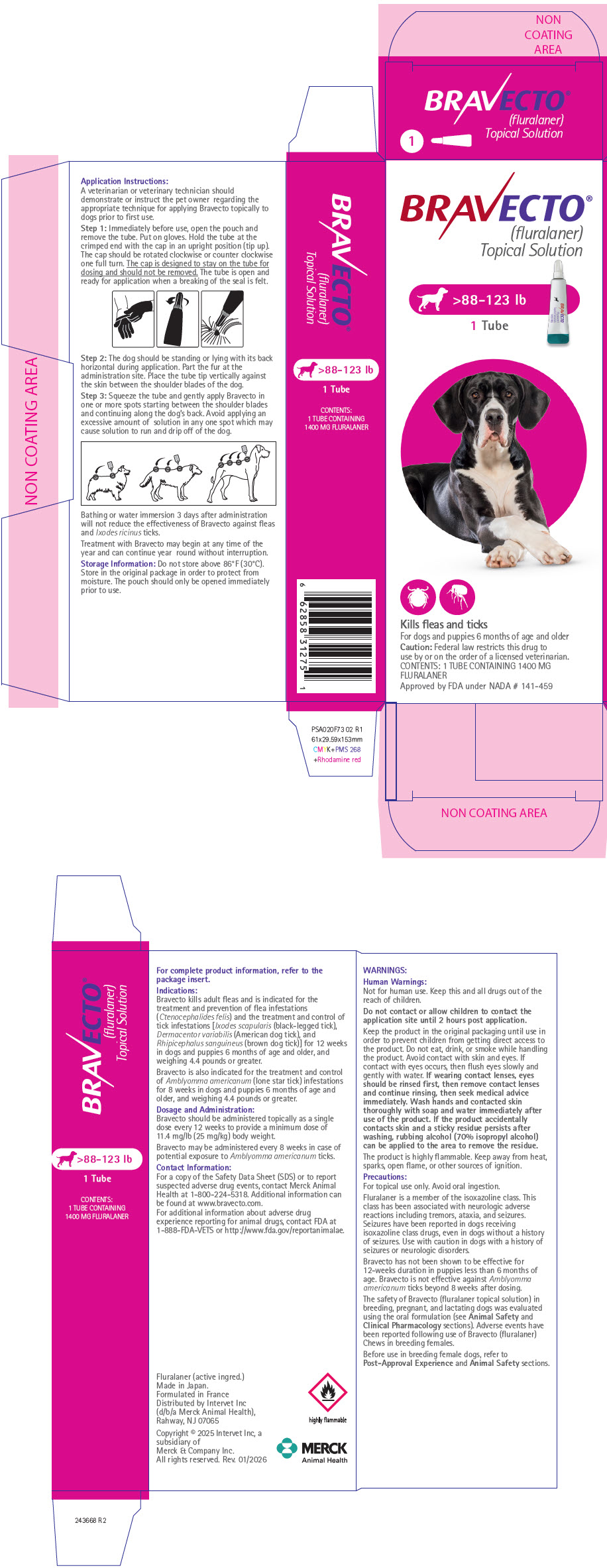 DRUG LABEL: Bravecto
NDC: 0061-5500 | Form: SOLUTION
Manufacturer: Merck Sharp & Dohme Corp.
Category: animal | Type: PRESCRIPTION ANIMAL DRUG LABEL
Date: 20260209

ACTIVE INGREDIENTS: FLURALANER 112.5 mg/1 1

BRAVECTO®
(fluralaner topical solution) for Dogs

Caution

Federal law restricts this drug to use by or on the order of a licensed veterinarian.

Description:

Each tube is formulated to provide a minimum dose of 11.4 mg/lb (25 mg/kg) body weight. Each milliliter contains 280 mg of fluralaner.

The chemical name of fluralaner is (±)-4-[5-(3,5-dichlorophenyl)-5-(trifluoromethyl)-4,5-dihydroisoxazol-3-yl]-2-methyl-N-[2-oxo-2-(2,2,2-trifluoroethylamino) ethyl]benzamide. Inactive ingredients: dimethylacetamide, glycofurol, diethyltoluamide, acetone

Indications:

Bravecto kills adult fleas and is indicated for the treatment and prevention of flea infestations (Ctenocephalides felis) and the treatment and control of tick infestations [Ixodes scapularis (black-legged tick), Dermacentor variabilis (American dog tick), and Rhipicephalus sanguineus (brown dog tick)] for 12 weeks in dogs and puppies 6 months of age and older, and weighing 4.4 pounds or greater.

Bravecto is also indicated for the treatment and control of Amblyomma americanum (lone star tick) infestations for 8 weeks in dogs and puppies 6 months of age and older, and weighing 4.4 pounds or greater.

Dosage and Administration:

Bravecto should be administered topically as a single dose every 12 weeks according to the Dosage Schedule below to provide a minimum dose of 11.4 mg/lb (25 mg/kg) body weight.

Bravecto may be administered every 8 weeks in case of potential exposure to Amblyomma americanum ticks (see Effectiveness).

Dosage Schedule
Body Weight Ranges (lb) | Fluralaner content (mg)/tube | Tubes Administered
4.4 – 9.9 | 112.5 | One
>9.9 – 22.0 | 250 | One
>22.0 – 44.0 | 500 | One
>44.0 – 88.0 | 1000 | One
>88.0 – 123.0 [Dogs over 123.0 lb should be administered the appropriate combination of tubes] | 1400 | One

A veterinarian or veterinary technician should demonstrate or instruct the pet owner regarding the appropriate technique for applying Bravecto topically to dogs prior to first use.

Step 1: Immediately before use, open the pouch and remove the tube. Put on gloves. Hold the tube at the crimped end with the cap in an upright position (tip up). The cap should be rotated clockwise or counter clockwise one full turn. The cap is designed to stay on the tube for dosing and should not be removed. The tube is open and ready for application when a breaking of the seal is felt.

Step 2: The dog should be standing or lying with its back horizontal during application. Part the fur at the administration site. Place the tube tip vertically against the skin between the shoulder blades of the dog.

Step 3: Squeeze the tube and gently apply Bravecto in one or more spots starting between the shoulder blades and continuing along the dog's back. Avoid applying an excessive amount of solution in any one spot which may cause some solution to run or drip off of the dog.

Bathing or water immersion 3 days after administration will not reduce the effectiveness of Bravecto against fleas and Ixodes ricinus ticks (see Effectiveness).

Treatment with Bravecto may begin at any time of the year and can continue year round without interruption.

Contraindications:

There are no known contraindications for the use of the product.

WARNINGS

Human Warnings:

Not for human use. Keep this and all drugs out of the reach of children.

Do not contact or allow children to contact the application site until 2 hours post application

Keep the product in the original packaging until use in order to prevent children from getting direct access to the product.

Do not eat, drink, or smoke while handling the product. Avoid contact with skin and eyes. If contact with eyes occurs, then flush eyes slowly and gently with water. If wearing contact lenses, eyes should be rinsed first, then remove contact lenses and continue rinsing, then seek medical advice immediately. Wash hands and contacted skin thoroughly with soap and water immediately after use of the product. If the product accidentally contacts skin and a sticky residue persists after washing, rubbing alcohol (70% isopropyl alcohol) can be applied to the area to remove the residue.

The product is highly flammable. Keep away from heat, sparks, open flame or other sources of ignition.

Precautions:

For topical use only. Avoid oral ingestion. (see Animal Safety).

Fluralaner is a member of the isoxazoline class. This class has been associated with neurologic adverse reactions including tremors, ataxia, and seizures. Seizures have been reported in dogs receiving isoxazoline class drugs, even in dogs without a history of seizures. Use with caution in dogs with a history of seizures or neurologic disorders.

Bravecto has not been shown to be effective for 12-weeks duration in puppies less than 6 months of age. Bravecto is not effective against Amblyomma americanum ticks beyond 8 weeks after dosing (see Effectiveness).

The safety of Bravecto (fluralaner topical solution) in breeding, pregnant, and lactating dogs was evaluated using the oral formulation (see Animal Safety and Clinical Pharmacology sections). Adverse events have been reported following use of Bravecto (fluralaner) Chews in breeding females.

Before use in breeding female dogs, refer to Post-Approval Experience and Animal Safety sections.

Adverse Reactions:

In a well-controlled U.S. field study, which included a total of 165 households and 321 treated dogs (221 with fluralaner and 100 with a topical active control), there were no serious adverse reactions.

Percentage of Dogs with Adverse Reactions in the Field Study
Adverse Reaction (AR) | Bravecto Group: Percent of Dogs with the AR During the 105-Day Study (n= 221 dogs) | Active Control Group: Percent of Dogs with the AR During the 84-Day Study (n= 100 dogs)
Vomiting | 6.3 % | 6.0 %
Alopecia | 4.1 % | 2.0 %
Diarrhea | 2.7 % | 11.0 %
Lethargy | 2.7 % | 2.0 %
Decreased Appetite | 1.4 % | 0.0 %
Moist Dermatitis/Rash | 0.9 % | 0.0 %

In the field study, two dogs treated with Bravecto with no prior history of seizures each experienced a seizure. One dog had two seizures a day apart about 18 days after its first dose. The dog was started on antiepileptic medication and had no additional seizures during the study. A second dog had a seizure 76 days after its first dose and 3 days after starting fluoxetine for separation anxiety. The fluoxetine was discontinued and the dog experienced no additional seizures during the study. One dog treated with Bravecto was observed by the owner to be off balance for about 30 minutes five days after its first dose and had no similar observations after the second dose. One dog with a history of seizures had a seizure the day after the second dose of the active control.

In two well-controlled laboratory dose confirmation studies, one dog developed mild to moderate redness, flaking, crusts/scabs and alopecia at the treatment site from Day 1 through 14 after application of Bravecto on Day 0, and one dog developed self-limiting generalized erythema (possible allergic reaction) one day after treatment with Bravecto.

In a European field study in cats, there were three reports of facial dermatitis in humans after close contact with the application site which occurred within 4 days of application.

Post-Approval Experience (2025):

The following adverse events are based on post-approval adverse drug experience reporting for Bravecto (fluralaner topical solution). Not all adverse events are reported to FDA/CVM. It is not always possible to reliably estimate the adverse event frequency or establish a causal relationship to product exposure using these data.

The following adverse events reported in dogs are listed in decreasing order of reporting frequency:

Lethargy, vomiting, application site disorders (including alopecia, pruritus, and erythema), behavioral changes (including hyperactivity and vocalization), anorexia/decreased appetite, seizure, diarrhea, generalized pruritus, tremors, and ataxia.

The following reproductive adverse events have been reported following use of Bravecto (fluralaner) Chews: birth defects (including limb deformities and cleft palate), stillbirth, and abortion.

Contact Information:

For a copy of the Safety Data Sheet (SDS) or to report suspected adverse drug events, contact Merck Animal Health at 1-800-224-5318. Additional information can be found at www.bravecto.com.

For additional information about adverse drug experience reporting for animal drugs, contact FDA at 1-888-FDA-VETS or http://www.fda.gov/reportanimalae.

Clinical Pharmacology:

Peak fluralaner concentrations are achieved between 7 and 42 days following topical administration and the elimination half-life ranges between 14 and 29 days. The bioavailability of fluralaner following oral and topical administration is approximately 25%.

Mode of Action:

Fluralaner is for systemic use and belongs to the class of isoxazoline-substituted benzamide derivatives. Fluralaner is an inhibitor of the arthropod nervous system. The mode of action of fluralaner is the antagonism of the ligand-gated chloride channels (gamma-aminobutyric acid (GABA)-receptor and glutamate-receptor).

Effectiveness:

In well-controlled laboratory studies, Bravecto killed fleas and reduced the numbers of live fleas on dogs by >99% and 100% within 24 and 48 hours, respectively, post-infestation for 12 weeks. In well-controlled laboratory studies, Bravecto demonstrated ≥93.3% effectiveness against Dermacentor variabilis, Ixodes scapularis and Rhipicephalus sanguineus 48 hours post-infestation for 12 weeks. Bravecto demonstrated ≥90% effectiveness against Amblyomma americanum 72 hours post-infestation for 8 weeks, but failed to demonstrate ≥90% effectiveness beyond 8 weeks.

In a well-controlled U.S. field study, a single dose of Bravecto reduced fleas by ≥99.8% for 12 weeks. Dogs with signs of flea allergy dermatitis showed improvement in erythema, alopecia, papules, scales, crusts, and excoriation as a direct result of eliminating flea infestations.

In a European laboratory study, Bravecto demonstrated ≥98.2% effectiveness against fleas and Ixodes ricinus ticks after multiple water immersion or shampooing occasions, the first occurring 3 days after application, for 12 weeks.

Animal Safety:

Margin of Safety Study: In a margin of safety study, Bravecto was administered topically to 8- to 9-week-old-puppies at 1, 3, and 5× the maximum labeled dose of 56 mg/kg at three, 8-week intervals (8 dogs per group). The dogs in the control group (0×) were administered mineral oil.

There were no clinically-relevant, treatment-related effects on physical examination, body weights, food consumption, clinical pathology (hematology, clinical chemistries, coagulation tests, and urinalysis), gross pathology, histopathology, or organ weights. Cosmetic changes at the application site included matting/clumping/spiking of hair, wetness, or a greasy appearance.

Oral Safety Study: In a safety study, one dose of Bravecto topical solution was administered orally to 8- to 10-month-old-puppies at 1× the maximum labeled dose of 56 mg/kg. The dogs in the control group (0×) were administered saline orally.

There were no clinically-relevant, treatment-related effects on physical examination, body weights, food consumption, clinical pathology (hematology, clinical chemistries, coagulation tests, and urinalysis), gross pathology, histopathology, or organ weights. Five of the six treated dogs experienced salivation immediately after administration. One treated animal experienced loose feces with blood three hours after administration. One treated animal experienced vomiting eight hours after administration.

Reproductive Safety: Reproductive safety was evaluated for Bravecto Chews, NADA 141-426 (see Clinical Pharmacology). Bravecto Chews were administered orally to intact, reproductively- sound male and female Beagles at a dose of up to 168 mg/kg (equivalent to 3× the maximum treatment dose) on three to four occasions at 8-week intervals. The dogs in the control group (0×) were untreated.

There were no clinically-relevant, treatment-related effects on the body weights, food consumption, reproductive performance, semen analysis, litter data, gross necropsy (adult dogs) or histopathology findings (adult dogs and puppies). One adult treated dog suffered a seizure during the course of the study (46 days after the third treatment). Abnormal salivation was observed on 17 occasions: in six treated dogs (11 occasions) after dosing and four control dogs (6 occasions).

The following abnormalities were noted in 7 pups from 2 of the 10 dams in only the treated group during gross necropsy examination: limb deformity (4 pups), enlarged heart (2 pups), enlarged spleen (3 pups), and cleft palate (2 pups). During veterinary examination at Week 7, two pups from the control group had inguinal testicles, and two and four pups from the treated group had inguinal and cryptorchid testicles, respectively. No undescended testicles were observed at the time of necropsy (days 50 to 71).

In a well-controlled field study Bravecto was used concurrently with other medications, such as vaccines, anthelmintics, antibiotics, steroids and sedatives.

Storage Information:

Do not store above 86°F (30°C). Store in the original package in order to protect from moisture. The pouch should only be opened immediately prior to use.

How Supplied:

Bravecto is available in five strengths for use in dogs (112.5, 250, 500, 1000, and 1400 mg fluralaner per tube). Each tube is packaged individually in a pouch. Product may be supplied in 1 or 2 tubes per carton.

Approved by FDA under NADA # 141-459

Distributed by:
Intervet, Inc., (d/b/a Merck Animal Health),
Rahway, NJ 07065

Fluralaner (active ingred.) Made in Japan.
Formulated in France

Copyright © 2025 Intervet Inc, a subsidiary of Merck &
Company Inc. All rights reserved.

Rev. 01/2026

243659 R3

PRINCIPAL DISPLAY PANEL - 112.5 MG Tube Carton

BRAVECTO®
(fluralaner)
Topical Solution

4.4-9.9 lb
1 Tube

Kills fleas and ticks
For dogs and puppies 6 months of age and older
Caution: Federal law restricts this drug to
use by or on the order of a licensed veterinarian.
CONTENTS: 1 TUBE CONTAINING 112.5 MG
FLURALANER

Approved by FDA under NADA # 141-459

PRINCIPAL DISPLAY PANEL - 250 MG Tube Carton

BRAVECTO®
(fluralaner)
Topical Solution

>9.9-22 lb
1 Tube

Kills fleas and ticks
For dogs and puppies 6 months of age and older
Caution: Federal law restricts this drug to
use by or on the order of a licensed veterinarian.
CONTENTS: 1 TUBE CONTAINING 250 MG
FLURALANER

Approved by FDA under NADA # 141-459

PRINCIPAL DISPLAY PANEL - 500 MG Tube Carton

BRAVECTO®
(fluralaner)
Topical Solution

>22-44 lb
1 Tube

Kills fleas and ticks
For dogs and puppies 6 months of age and older
Caution: Federal law restricts this drug to
use by or on the order of a licensed veterinarian.
CONTENTS: 1 TUBE CONTAINING 500 MG
FLURALANER

Approved by FDA under NADA # 141-459

PRINCIPAL DISPLAY PANEL - 1000 MG Tube Carton

BRAVECTO®
(fluralaner)
Topical Solution

>44-88 lb
1 Tube

Kills fleas and ticks
For dogs and puppies 6 months of age and older
Caution: Federal law restricts this drug to
use by or on the order of a licensed veterinarian.
CONTENTS: 1 TUBE CONTAINING 1000 MG
FLURALANER

Approved by FDA under NADA # 141-459

PRINCIPAL DISPLAY PANEL - 1400 MG Tube Carton

BRAVECTO®
(fluralaner)
Topical Solution

>88-123 lb
1 Tube

Kills fleas and ticks
For dogs and puppies 6 months of age and older
Caution: Federal law restricts this drug to
use by or on the order of a licensed veterinarian.
CONTENTS: 1 TUBE CONTAINING 1400 MG
FLURALANER

Approved by FDA under NADA # 141-459